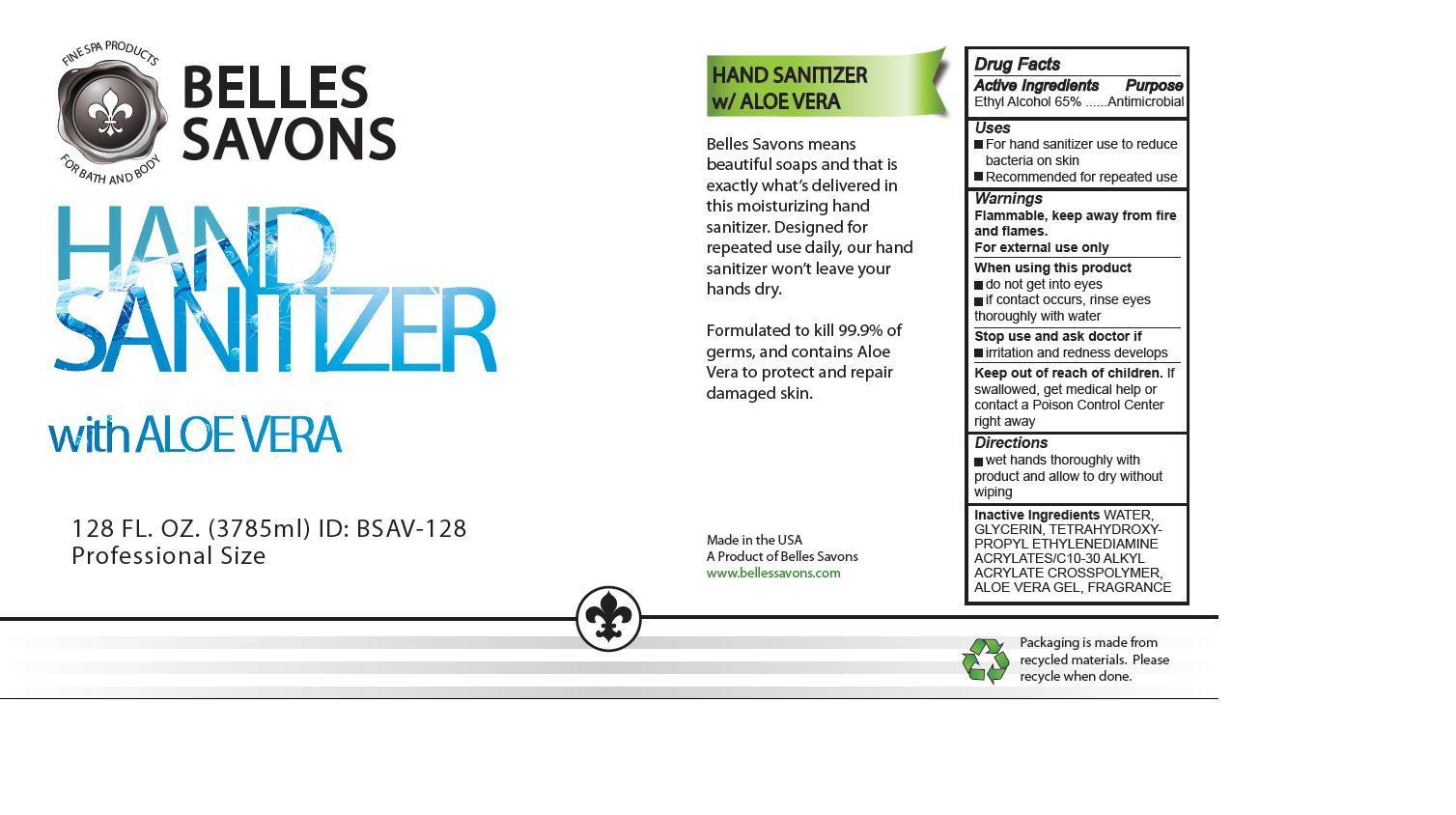 DRUG LABEL: HAND SANITIZER with ALOE VERA
NDC: 60717-001 | Form: LIQUID
Manufacturer: RNA PHARMA LLC
Category: otc | Type: HUMAN OTC DRUG LABEL
Date: 20141031

ACTIVE INGREDIENTS: ALCOHOL 65 mL/1 mL
INACTIVE INGREDIENTS: WATER; GLYCERIN; EDETOL; CARBOMER INTERPOLYMER TYPE B (ALLYL PENTAERYTHRITOL CROSSLINKED); ALOE VERA LEAF

HAND SANITIZER with ALOE VERA

Drug Facts

Active ingredient

ETHYL ALCOHOL 65%

Purpose

Antimicrobial

Uses

- For hand sanitizer use to reduce bacteria on skin
- Recommended for repeated use

Warnings

When using this product

- do not get into eyes
- if contact occurs, rinse eyes thoroughly with water

Stop use and ask a doctor if

- irritation and redness develops

Keep out of the reach of children

If swallowed, get medical help or contact a Poison Control Center right away

Directions

- wet hands thoroughly with product and allow to dry without wiping

Inactive ingredients

WATER, GLYCERIN, TETRAHYDROXYPROPYL ETHYLENEDIAMINE, ACRYLATES/C10-30 ALKYL ACRYLATE CROSSPOLYMER,

ALOE VERA GEL, FRAGRANCE

PRINCIPAL DISPLAY PANEL - 3785 mL Bottle Label

NDC 60717-001-01

HAND SANITIZER with ALOE VERA

128 FL. OZ. (3785 mL)